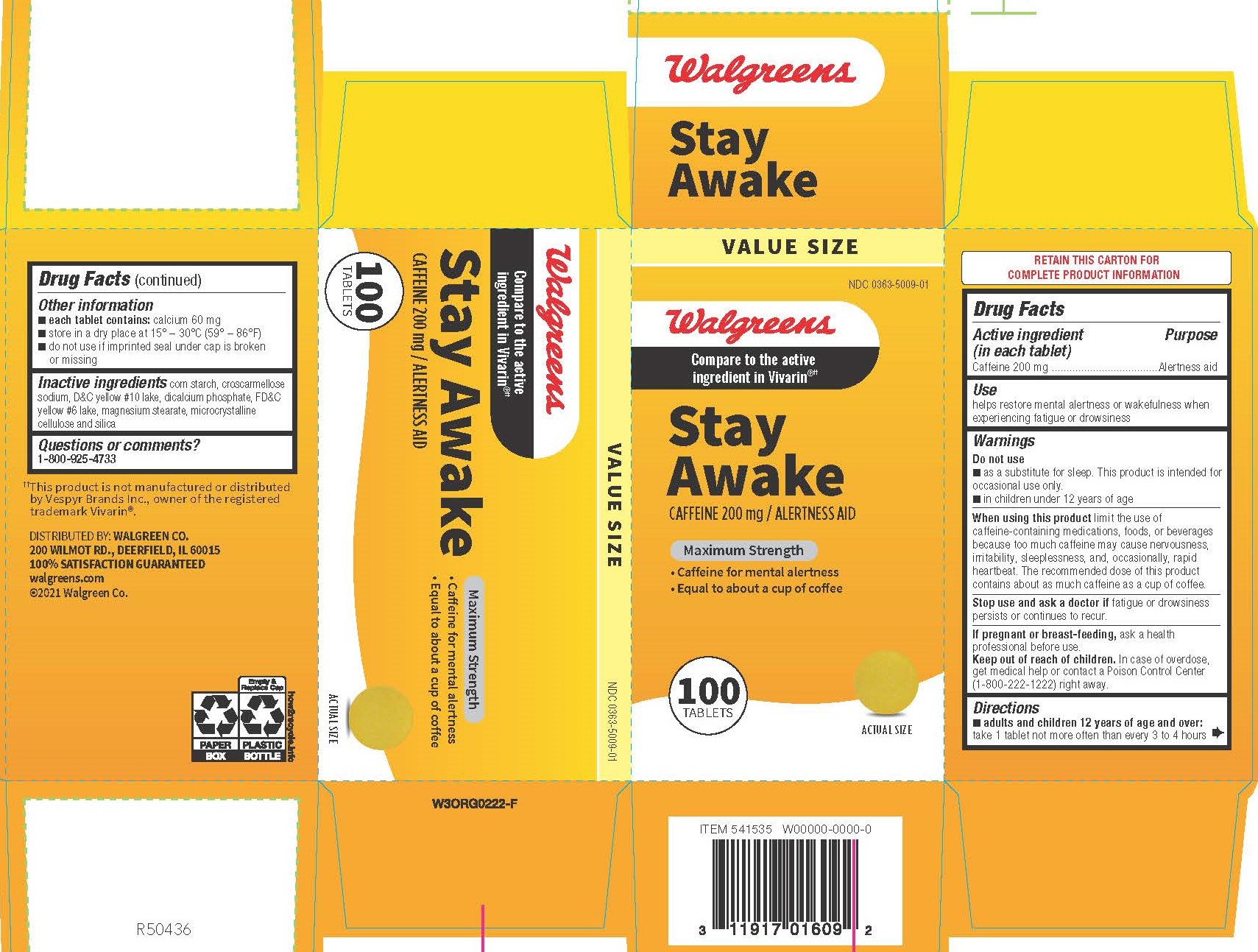 DRUG LABEL: Caffeine
NDC: 0363-5009 | Form: TABLET
Manufacturer: Walgreen Company
Category: otc | Type: HUMAN OTC DRUG LABEL
Date: 20241206

ACTIVE INGREDIENTS: CAFFEINE 200 mg/1 1
INACTIVE INGREDIENTS: STARCH, CORN; MAGNESIUM STEARATE; MICROCRYSTALLINE CELLULOSE; DIBASIC CALCIUM PHOSPHATE DIHYDRATE; SILICON DIOXIDE; FD&C YELLOW NO. 6; CROSCARMELLOSE SODIUM; D&C YELLOW NO. 10

5009 - Walgreen

Drug Facts

Active ingredient (in each tablet)
Caffeine 200 mg

Purpose
Alertness aid

Use

helps restore mental alertness or wakefulness when experiencing fatigue or drowsiness

WARNINGS

Do not use
■ as a substitute for sleep. This product is intended for occasional use only.
■ in children under 12 years of age

When using this product limit the use of caffeine-containing medications, foods, or beverages because too much caffeine may cause nervousness, irritability, sleeplessness, and, occasionally, rapid heartbeat. The recommended dose of this product contains about as much caffeine as a cup of coffee.

Stop use and ask a doctor if fatigue or drowsiness persists or continues to recur.

PREGNANCY OR BREAST FEEDING

If pregnant or breast-feeding, ask a health professional before use.

Keep out of reach of children.

OVERDOSAGE

In case of overdose, get medical help or contact a Poison Control Center (1-800-222-1222) right away.

Directions

■ adults and children 12 years of age and over: take 1 tablet not more often than every 3 to 4 hours

Other Information

■ each tablet contains: calcium 60 mg
■ store in a dry place at 15° – 30°C (59° – 86°F)
■ do not use if imprinted seal under cap is broken or missing

INACTIVE INGREDIENT

corn starch, croscarmellose sodium, D&C yellow #10 lake, dicalcium phosphate, FD&C yellow #6 lake, magnesium stearate, microcrystalline cellulose and silica

Questions or comments?

1-800-925-4733

DISTRIBUTED BY:
WALGREEN CO.
200 WILMOT ROAD
DEERFIELD, IL 60015

PACKAGE LABEL

Walgreens

Compare to Vivarin® active ingredient††

Stay Awake

CAFFEINE 200 mg /
ALERTNESS AID

Maximum Strength

• Caffeine for mental alertness
• Equal to about a cup of coffee

100 Tablets